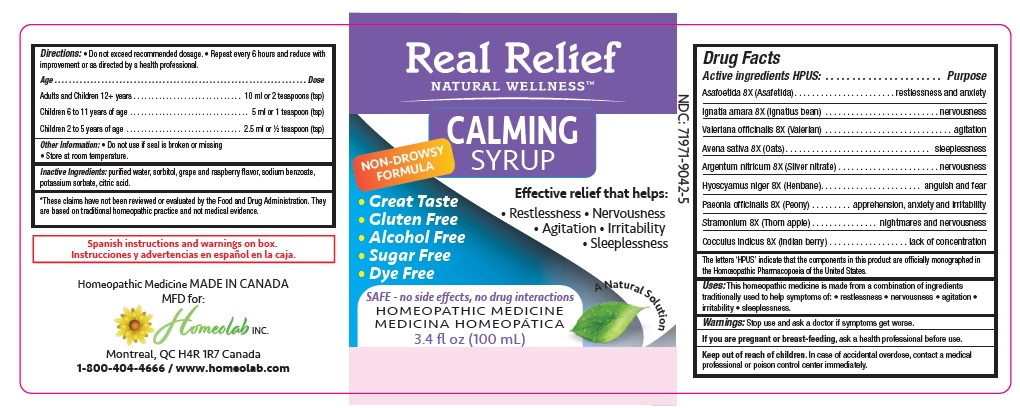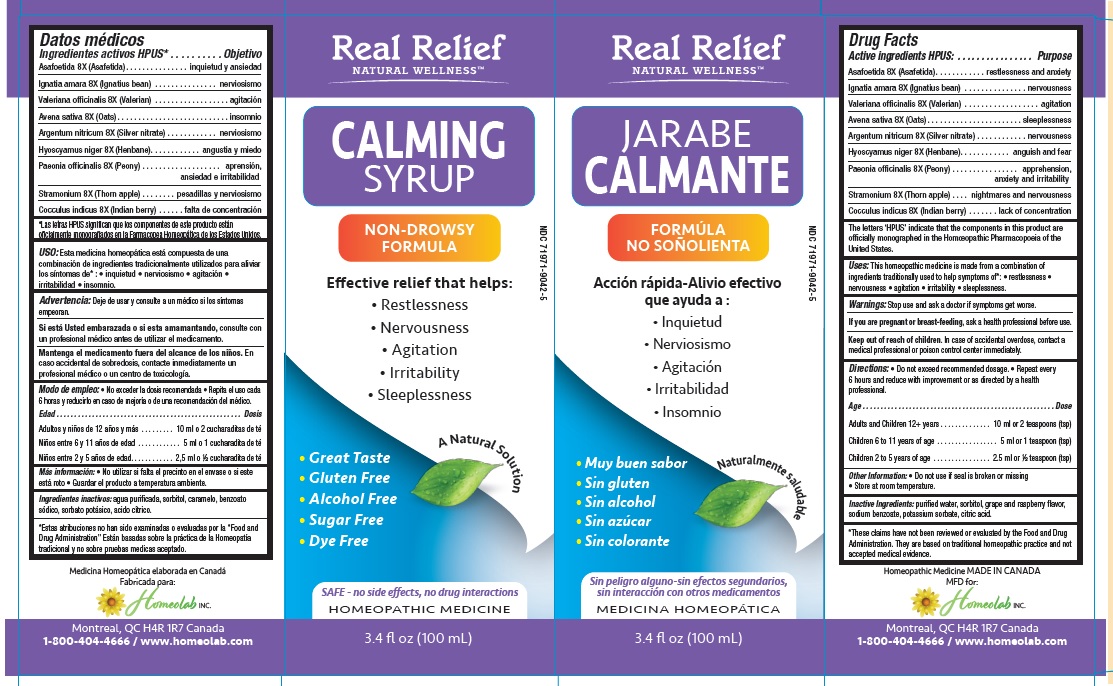 DRUG LABEL: Real Relief Natural Wellness Calming Syrup
NDC: 71971-9042 | Form: LIQUID
Manufacturer: Homeolab International (Canada) inc
Category: homeopathic | Type: HUMAN OTC DRUG LABEL
Date: 20221103

ACTIVE INGREDIENTS: FERULA ASSA-FOETIDA RESIN 8 [hp_X]/100 mL; STRYCHNOS IGNATII SEED 8 [hp_X]/100 mL; VALERIANA OFFICINALIS WHOLE 8 [hp_X]/100 mL; OAT BRAN 8 [hp_X]/100 mL; SILVER NITRATE 8 [hp_X]/100 mL; HYOSCYAMUS NIGER 8 [hp_X]/100 mL; PAEONIA OFFICINALIS ROOT 8 [hp_X]/100 mL; DATURA STRAMONIUM 8 [hp_X]/100 mL; ANAMIRTA COCCULUS WHOLE 8 [hp_X]/100 mL
INACTIVE INGREDIENTS: WATER; SORBITOL; CARAMEL; SODIUM BENZOATE; POTASSIUM SORBATE; CITRIC ACID MONOHYDRATE

Active Ingredients

ASAFOETIDA (ASAFETIDA) 8 [hp-X]

IGNATIA AMARA (IGNATUS BEAN) 8 [hp-X]

VALERIANA OFFICINALIS (VALERIAN) 8 [hp-X]

AVENA SATIVA (OAT) 8 [hp-X]

ARGENTUM NITRICUM (SILVER NITRATE) 8 [hp-X]

HYOSCYAMUS NIGER (HENBANE) 8 [hp-X]

PAEONIA OFFICINALIS (PEONY) 8 [hp-X]

STRAMONIUM (THORN APPLE) 8 [hp-X]

ANCOCCULUS INDICUS (INDIAN BERRY) 8 [hp-X]

The letters 'HPUS' indicate that the compo nents in this pro duct are o fficially mo no g raphed in the Ho mo eo pathic Pharmaco po eia o f the United States.

Purpose

ASAFOETIDA Restlessness and Anxiety

IGNATIA AMARA Nervousness

VALERIANA OFFICINALIS Agitation

AVENA SATIVA Sleeplessness

ARGENTUM NITRICUM Nervousness

ARGENTUM NITRICUM Nervousness

HYOSCYAMUS NIGER Anguish and fear

PAEONIA OFFICINALIS Apprehension, anxiety and irritability

STRAMONIUM Nightmares and nervousness

COCCULUS INDICUS Lack of concentration

Uses

This homeopathic medicine is made from a combination of ingredients traditionally used to help relieve symptoms of*: restlessness, nervousness, irritability, agitation, sleeplessness, lessen nightmares.

*These claims have not been reviewed by the Food and Drug Administration. They are based on traditional homeopathic practice, not medical evidence.

Warnings

Stop use and ask a doctor if symptoms worsen:

If you are pregnant or breast feeding, ask a health professional before.

Keep out of reach of children. In case of accidental overdose, contact a medical
professional or poison control center immediately.

Directions

• Do not exceed recommended dosage

• Repeat every 6 hours and reduce with improvement or as directed by a health professional.
Age………………………………………………………….................Dose
Adults and Children 12 + years. ............................................10 ml or 2 teaspoon (tsp)
Children 6 to 11 years of age. ...............................................5 ml or 1 teaspoon (tsp)
Children 2 to 5 years of age. .................................................2.5 ml or ½ teaspoon (tsp)

Other information

Store at room temperature.• Do not use if seal is broken or missing

*These claims have not been reviewed by the Food and Drug Administration. They are based on traditional homeopathic practice, not medical evidence.

Inactive ingredients

Purified water, sorbitol, grape and raspberry flavor, sodium benzoate, potassium sorbate, citric acid.